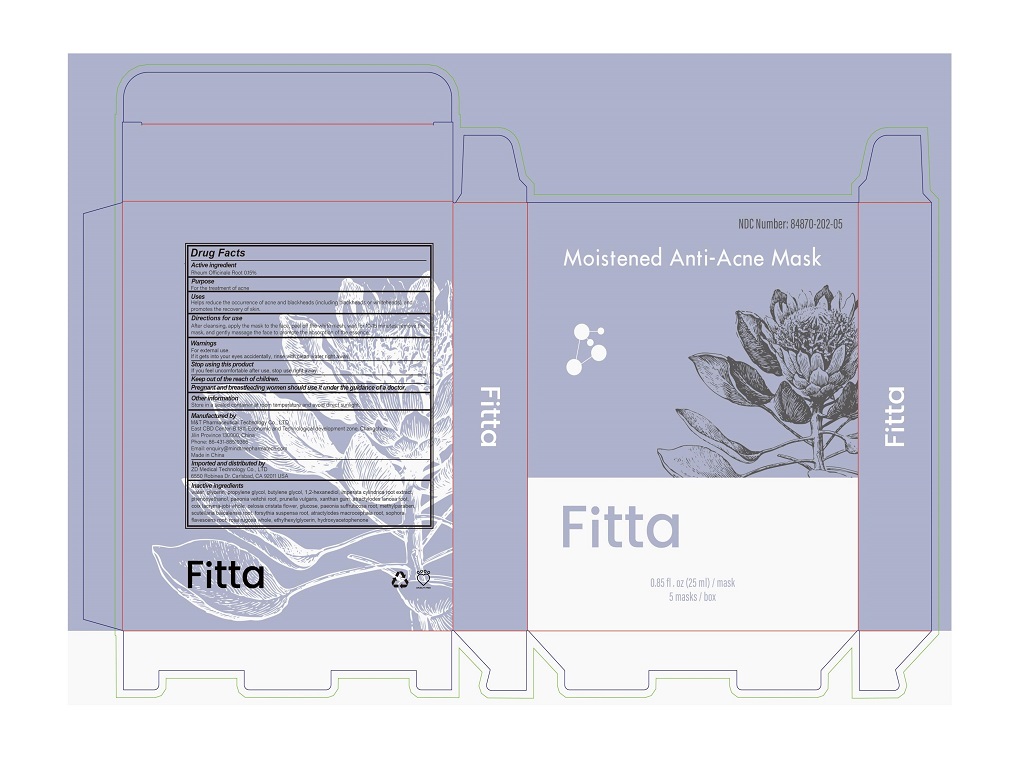 DRUG LABEL: MoistiMed Anti-Acne Mask
NDC: 84870-202 | Form: POULTICE
Manufacturer: M&T Pharmaceutical Technology Co.,LTD
Category: otc | Type: HUMAN OTC DRUG LABEL
Date: 20251218

ACTIVE INGREDIENTS: RHEUM OFFICINALE ROOT 0.15 g/0.15 mL
INACTIVE INGREDIENTS: WATER; GLYCERIN; PROPYLENE GLYCOL; BUTYLENE GLYCOL; 1,2-HEXANEDIOL; IMPERATA CYLINDRICA ROOT; PHENOXYETHANOL; PAEONIA VEITCHII ROOT; PRUNELLA VULGARIS; XANTHAN GUM; ATRACTYLODES LANCEA ROOT; COIX LACRYMA-JOBI WHOLE; CELOSIA CRISTATA FLOWER; GLUCOSE; PAEONIA SUFFRUTICOSA ROOT; METHYLPARABEN; SCUTELLARIA BAICALENSIS ROOT; FORSYTHIA SUSPENSA ROOT; ATRACTYLODES MACROCEPHALA ROOT; SOPHORA FLAVESCENS ROOT; ROSA RUGOSA WHOLE; ETHYLHEXYLGLYCERIN; HYDROXYACETOPHENONE

M&T Pharmaceutical Technology Co., LTD

Active Ingredient

Rheum Officinale Root 0.15%

Purpose

For the treatment of acne

Uses

Helps reduce the occurrence of acne and blackheads (including blackheads or whiteheads), and promotes the recovery of skin.

Directions for use

After cleansing, apply the mask to the face, peel off the white mesh, wait for 10-15 minutes, remove the mask, and gently massage the face to promote the absorption of the essence.

Warnings

- For external use.
- If it gets into your eyes accidentally, rinse with clean water immediately.

Stop using this product

If you feel uncomfortable after use, please stop using it immediately.

Storage conditions

Store in a sealed container at room temperature and avoid direct sunlight.

Manufactured by M&T Pharmaceutical Technology Co.,LTD.

East CBD Center-B 1811, Economic and Technological development zone, Changchun, Jilin Province 130000, China
Phone: 86-431-88519366
Email: enquiry@mindtreepharmatech.com

Made in China

Imported and Distributed by

ZD Medical Technology Co., Ltd
6550 Robinea Dr. Carlsbad, CA 92011 USA